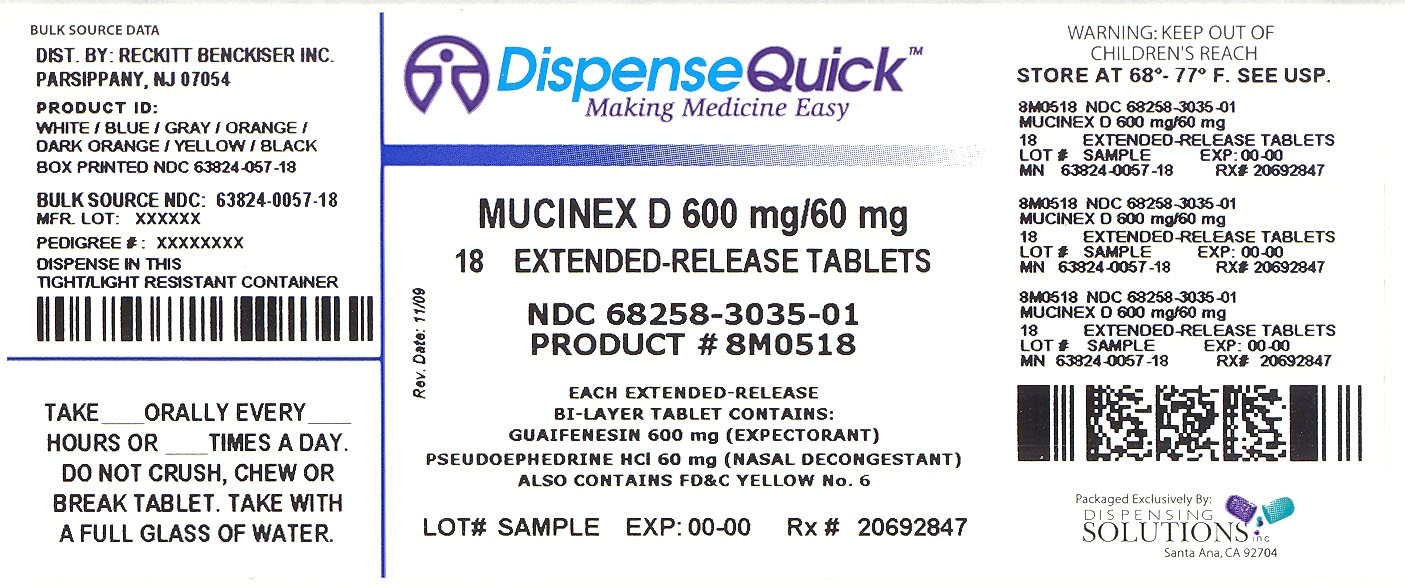 DRUG LABEL: Mucinex D
NDC: 68258-3035 | Form: TABLET, EXTENDED RELEASE
Manufacturer: Dispensing Solutions Inc.
Category: prescription | Type: HUMAN PRESCRIPTION DRUG LABEL
Date: 20100302

ACTIVE INGREDIENTS: GUAIFENESIN 600 mg/1 1; PSEUDOEPHEDRINE HYDROCHLORIDE 60 mg/1 1

Mucinex®D

Drug Facts

ACTIVE INGREDIENT

PURPOSE

Active ingredients (in each extended-release bi-layer tablet) | Purpose
Guaifenesin 600 mg | Expectorant
Pseudoephedrine HCl 60 mg | Nasal Decongestant

Uses

- helps loosen phlegm (mucus) and thin bronchial secretions to rid the bronchial passageways of bothersome mucus and make coughs more productive
- temporarily relieves nasal congestion due to:
  - common cold
  - hay fever
  - upper respiratory allergies
- temporarily restores freer breathing through the nose
- promotes nasal and/or sinus drainage
- temporarily relieves sinus congestion and pressure

Warnings

Do not use if you are now taking a prescription monoamine oxidase inhibitor (MAOI) (certain drugs for depression, psychiatric or emotional conditions, or Parkinson's disease), or for 2 weeks after stopping the MAOI drug. If you do not know if your prescription drug contains an MAOI, ask a doctor or pharmacist before taking this product.

Ask a doctor before use if you have

- heart disease
- high blood pressure
- thyroid disease
- diabetes
- trouble urinating due to an enlarged prostate gland
- persistent or chronic cough such as occurs with smoking, asthma, chronic bronchitis, or emphysema
- cough accompanied by too much phlegm (mucus)

When using this product

- do not use more than directed

Stop use and ask a doctor if

- you get nervous, dizzy, or sleepless
- symptoms do not get better within 7 days, come back or occur with a fever, rash, or persistent headache. These could be signs of a serious illness.

PREGNANCY OR BREAST FEEDING

If pregnant or breast-feeding, ask a health professional before use.

Keep out of reach of children. In case of overdose, get medical help or contact a Poison Control Center right away.

Directions

- do not crush, chew, or break tablet
- take with a full glass of water
- this product can be administered without regard for timing of meals
- adults and children 12 years and older: 2 tablets every 12 hours; not more than 4 tablets in 24 hours
- children under 12 years of age: do not use

Other information

- tamper evident: do not use if carton is open or if printed seal on blister is broken or missing
- store at 20-25°C (68-77°F)

Inactive ingredients

carbomer 934P, NF; FD&C yellow #6 aluminum lake; hypromellose, USP; magnesium stearate, NF; microcrystalline cellulose, NF; sodium starch glycolate, NF

How Supplied

Mucinex®D is supplied by Dispensing Solutions Inc. as follows:

NDC | Strength | Quantity/Form | Color | Source NDC
68258-3035-1 | 600 mg / 60 mg | 18 Tablets | WHITE | 63824-057-18

This product was:

Distributed by:
Reckitt Benckiser Inc.
Parsippany, NJ 07054-0224

And Relabeled By:

Dispensing Solutions Inc.
3000 West Warner Ave
Santa Ana, CA 92704
United States

PRINCIPAL DISPLAY PANEL - 600 mg Carton

NDC 68258-3035-1

Mucinex®D

600 mg guaifenesin & 60 mg pseudoephedrine HCl
extended-release bi-layer tablets

EXPECTORANT & NASAL DECONGESTANT

12 HOUR

NEW LOOK-
SAME RELIEF

Thins And Loosens Mucus

Clears Nasal/Sinus Congestion

18 EXTENDED-RELEASE BI-LAYER TABLETS